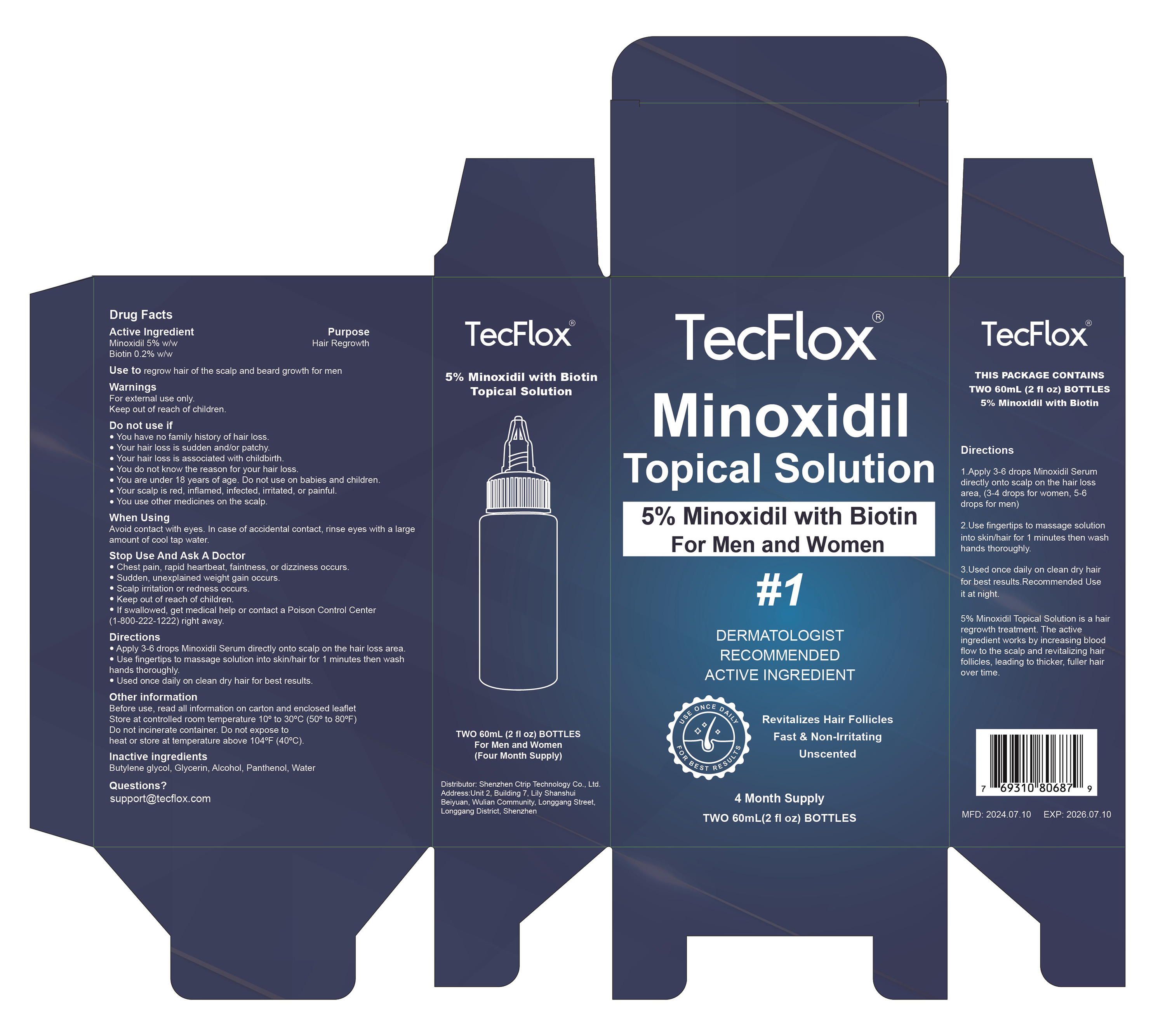 DRUG LABEL: 5% MINOXIDIL HAIR REGROWTH SERUM With Biotin
NDC: 84614-001 | Form: SOLUTION
Manufacturer: Shenzhen Ctrip Technology Co., Ltd.
Category: otc | Type: HUMAN OTC DRUG LABEL
Date: 20250912

ACTIVE INGREDIENTS: MINOXIDIL 5 g/100 mL; BIOTIN 0.2 g/100 mL
INACTIVE INGREDIENTS: GLYCERIN; WATER; ALCOHOL; BUTYLENE GLYCOL; PANTHENOL

84614-001 5% MINOXIDIL HAIR REGROWTH SERUM With Biotin

5% MINOXIDIL HAIR REGROWTH SERUM With Biotin

ACTIVE INGREDIENT

Minoxidil 5%
Biotin 0.2%

PURPOSE

Hair Regrowth

INDICATIONS AND USAGE

Use to regrow hair of the scalp and beard growth for men

WARNINGS

For external use only.
Keep out of reach of children.

DO NOT USE

You have no family history of hair loss.Your hair loss is sudden and/or patchy.
Your hair loss is associated with childbirth.
You do not know the reason for your hair loss.
You are under 18 years of age. Do not use on babies and children.
Your scalp is red, inflamed, infected, irritated, or painful.
You use other medicines on the scalp

WHEN USING

Avoid contact with eyes. In case of accidental contact, rinse eyes with a large amount of cool tap water.

STOP USE

Chest pain, rapid heartbeat, faintness, or dizziness occurs.
Sudden, unexplained weight gain occurs.
Scalp irritation or redness occurs.
Keep out of reach of children.
If swallowed, get medical help or contact a Poison Control Center (1-800-222-1222)right away.

Keep out of reach of children.
If swallowed, get medical help or contact a Poison Control Center (1-800-222-1222)right away.

DOSAGE AND ADMINISTRATION

Apply 3-6 drops Minoxidil Serum directly onto scalp on the hair loss area
Use fingertips to massage solution into skin/hair for 1 minutes then washhands thoroughly.
Used once daily on clean dry hair for best results

STORAGE AND HANDLING

Before use, read all information on carton and enclosed leafletStore at controlled room temperature 10° to 30°C (50° to 80°F)Do not incinerate container. Do not expose toheat or store at temperature above 104°F(40°C)

INACTIVE INGREDIENT

Butylene Glycol
Glycerin
Alcohol
Panthenol
Water